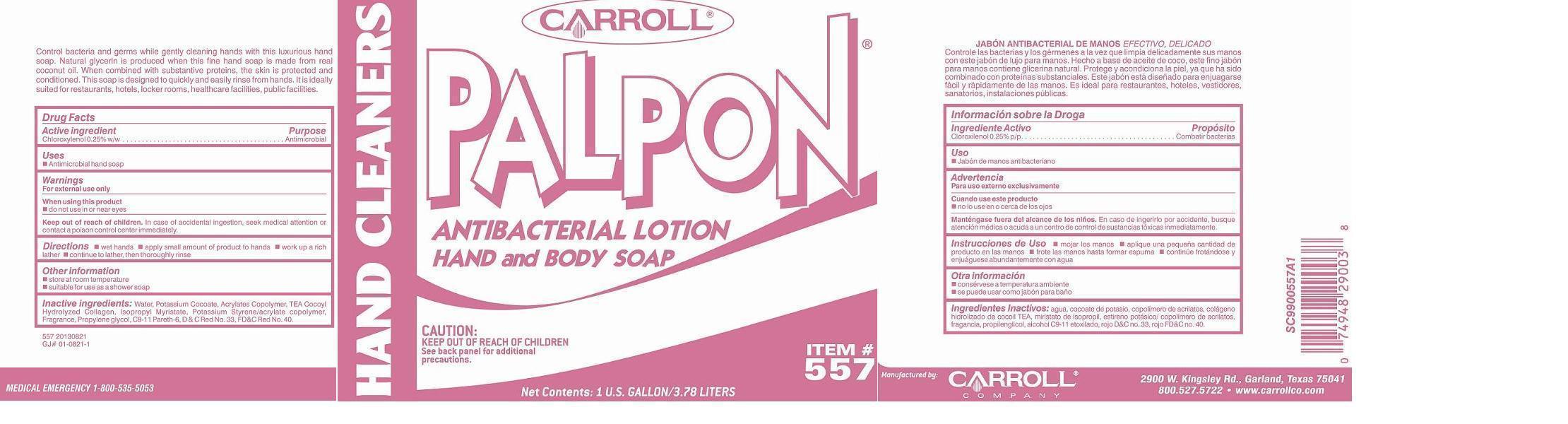 DRUG LABEL: PC557 PALPON
NDC: 10685-557 | Form: SOAP
Manufacturer: CARROLL COMPANY
Category: otc | Type: HUMAN OTC DRUG LABEL
Date: 20181231

ACTIVE INGREDIENTS: CHLOROXYLENOL 2.5 g/1000 mL
INACTIVE INGREDIENTS: WATER; ETHYL ACRYLATE/METHACRYLIC ACID/STEARETH-20 METHACRYLATE COPOLYMER; POTASSIUM COCOATE; PROPYLENE GLYCOL; ISOPROPYL MYRISTATE; C9-11 PARETH-6

Active ingredient

Chloroxylenol 0.25% w/w

Purpose

Antimicrobial

Keep out of reach of children

In case of accidental ingestion, seek medical attention or contact a poison control center immediately.

Uses

 Antimicrobial hand soap

Warnings

For external use only

When using this product

- do not use in or near eyes

Directions

 wet hands  apply small amount of product to hands  work up a rich lather  continue to lather, then thoroughly rinse.

Other information

 store at room temperature

 suitable for use as a shower soap

Inactive ingredients:

Water, Potassium Cocoate, Acrylates Copolymer, TEA Cocoyl Hydrolyzed Collagen, Isopropyl Myristate, Potassium Styrene/acrylate copolymer, Fragrance, Propylene Glycol, C9-11 Pareth-6, D&C Red No. 33, FD&C Red No. 40.